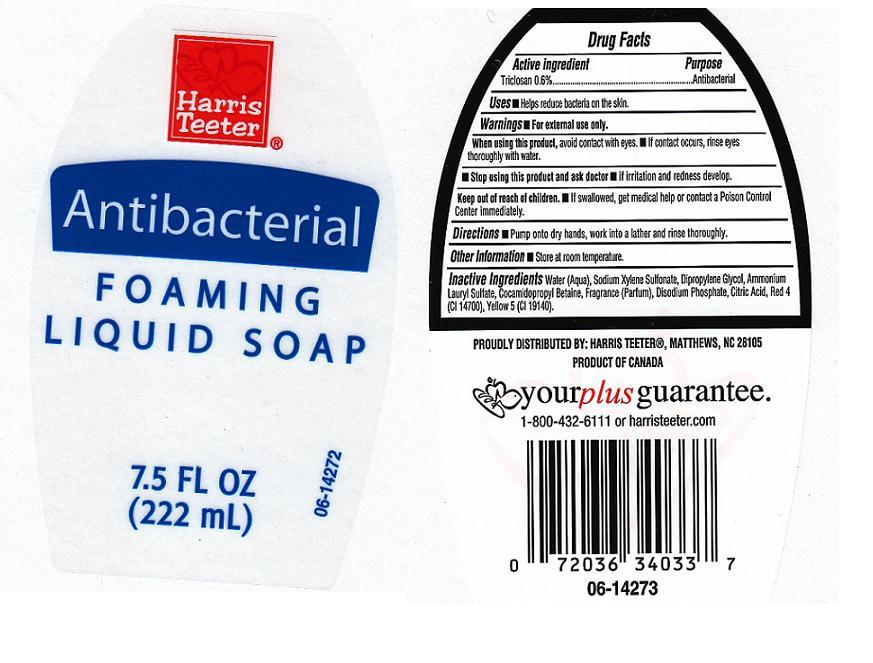 DRUG LABEL: Harris Teeter
NDC: 72036-168 | Form: SOAP
Manufacturer: Harris Teeter
Category: otc | Type: HUMAN OTC DRUG LABEL
Date: 20101007

ACTIVE INGREDIENTS: TRICLOSAN 0.6 mL/100 mL
INACTIVE INGREDIENTS: WATER; SODIUM POLYSTYRENE SULFONATE; DIPROPYLENE GLYCOL; AMMONIUM LAURYL SULFATE; COCAMIDOPROPYL BETAINE; SODIUM PHOSPHATE, DIBASIC, DIHYDRATE; CITRIC ACID MONOHYDRATE; FD&C RED NO. 4; FD&C YELLOW NO. 5

Active Ingredient

Triclosan 0.6%

Purpose

Antibacterial

Warnings

For external use only.

When using this product

- Avoid contact with eyes. If contact occurs, rinse with water.

Stop using this product and ask doctor if

- irritation or redness develops and lasts.

Keep out of reach of children

In case of accidental ingestion, get medical help or contact a Poison Control Center immediately.

Directions

Pump onto dry hands, work vigorously into a lather and rinse thoroughly.

Uses

Helps to decrease bacteria on the skin

Inactive Ingredients

Water (Aqua), Sodium Xylenesulfonate, Dipropylene Glycol, Ammonium Lauryl Sulfate, Cocamidopropyl Betaine, Fragrance(Parfum), Disodium Phosphate, Citric Acid,Yellow 5 (CI 19140), Red 40 (CI 16035).

Package Front and Back Labels

ht.jpg